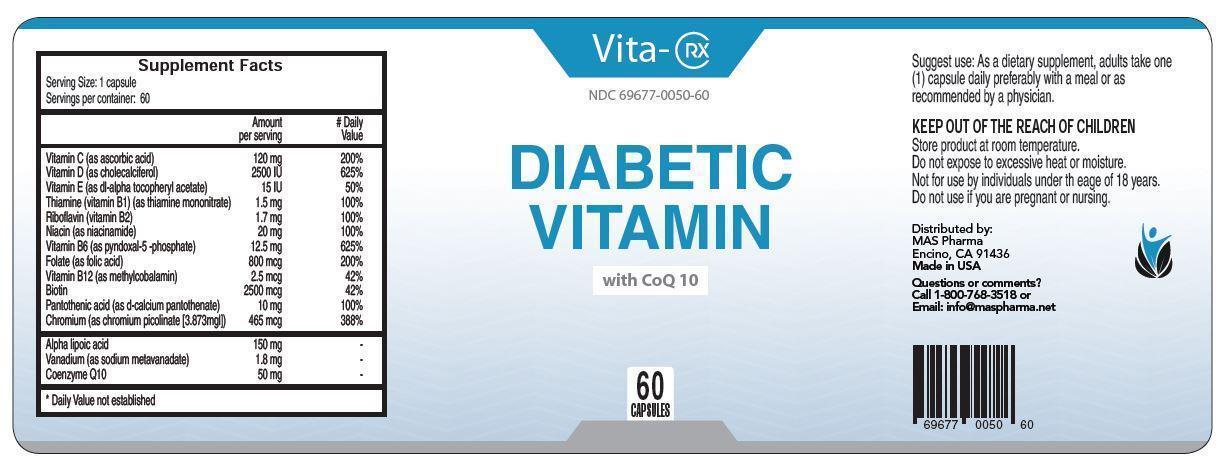 DRUG LABEL: Vita-Rx Diabetic Vitamin
NDC: 65121-301 | Form: CAPSULE, GELATIN COATED
Manufacturer: Pure Source, LLC
Category: prescription | Type: HUMAN PRESCRIPTION DRUG LABEL
Date: 20231122

ACTIVE INGREDIENTS: ASCORBIC ACID 120 mg/1 1; CHOLECALCIFEROL 0.0625 mg/1 1; .ALPHA.-TOCOPHEROL ACETATE 10 mg/1 1; THIAMINE MONONITRATE 1.5 mg/1 1; RIBOFLAVIN 1.7 mg/1 1; NIACIN 20 mg/1 1; PYRIDOXAL PHOSPHATE ANHYDROUS 12.5 mg/1 1; FOLIC ACID 0.8 mg/1 1; METHYLCOBALAMIN 0.0025 mg/1 1; BIOTIN 2.5 mg/1 1; CALCIUM PANTOTHENATE 10 mg/1 1; CHROMIUM PICOLINATE 0.465 mg/1 1; THIOCTIC ACID 150 mg/1 1; UBIDECARENONE 50 mg/1 1
INACTIVE INGREDIENTS: SODIUM METAVANADATE TETRAHYDRATE 1.8 mg/1 1; GELATIN; CELLULOSE, MICROCRYSTALLINE; MAGNESIUM STEARATE; SILICON DIOXIDE

Vita-Rx Diabetic Vitamin

DESCRIPTION

Vita-Rx

Diabetic Vitamin

with CoQ 10

INDICATIONS AND USAGE

Suggest use: As a dietary supplement, adults take one (1) capsule daily preferably with a meal or as recommended by a physician.

WARNINGS AND PRECAUTIONS

KEEP OUT OF THE REACH OF CHILDREN

Store product at room temperature.

Do not expose to excessive heat or moisture.

Not for use by individuals under th eage of 18 years.

Do not use if you are pregnant or nursing.

DOSAGE AND ADMINISTRATION

Suggest use: As a dietary supplement, adults take one (1) capsule daily preferably with a meal or as recommended by a physician.